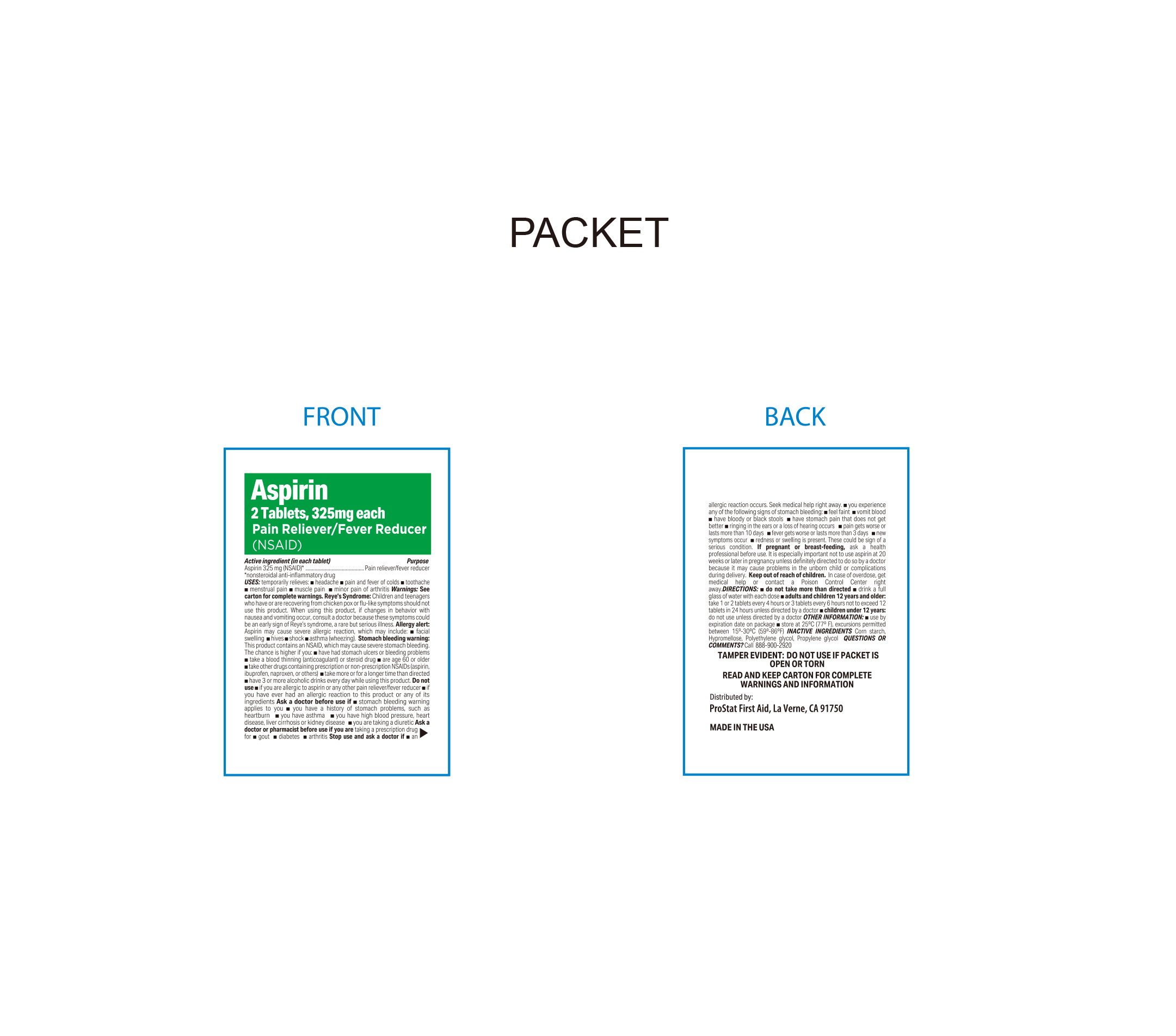 DRUG LABEL: Aspirin
NDC: 58228-0071 | Form: TABLET
Manufacturer: PROSTAT FIRST AID
Category: otc | Type: HUMAN OTC DRUG LABEL
Date: 20250808

ACTIVE INGREDIENTS: ASPIRIN 325 mg/1 1
INACTIVE INGREDIENTS: STARCH, CORN; HYPROMELLOSE, UNSPECIFIED; PROPYLENE GLYCOL; POLYETHYLENE GLYCOL, UNSPECIFIED

PROSTAT Aspirin 325mg (NSAID)
*nonsterhoidal anti-inflammatory drug

Active Ingredient

Aspirin 325mg (NSAID)

Nonsteroidal anti-inflammatory drug

Purpose

Pain Reliever / Fever Reducer

Do Not Use

- If you are allergic to aspirin or any other pain releiver / fever reducer
- If you have ever had an allergic reaction to this product or any of its ingredients

Uses

Temporarily relieves:

Headache

Pain and fever of colds

toothache

menstrual pain

muscle pain

minor pain of arthritis

Warnings

Reye's Syndrome

Children and teenagers who have or are recovering from chicken pox or flu-like symptoms should not use this product. When using this product, if changes in behaviour with nausea and vomiting occur, consult a doctor because these symptoms could be an early sign of Reye's Syndrome, a reare but serious illness.

Allergy Alert

Aspirin may cause severe allergic reaction, which may include, facial swelling, hives, shock, asthma (wheezing).

Stomach bleeding warning

This product contains an NSAID which may cause severe stomach bleeding. The chance is higher if you

- Have had stomach ulcers or bleeding problems
- Take blood thinning (anticogulant) or steroid drug
- Are age 60 or older
- take other drugs containing prescription or non-prescription NSAIDs (aspirin, ibuprofen, naproxen or others)
- Take more or for a longer time than directed
- Have 3 or more alcoholic drinks every day while using this product

Ask a doctor before use if

- Stomach bleeding warning applies to you.
- You have a history of stomach problems, such as heartburn
- You have asthma
- You have high blood pressure, heart disease, liver cirrhosis or kidney disease.
- You are taking a diuretic

Ask a doctor or pharmacist before use if you are

taking a prescription drug for gout, diabetes, arthritis

Directions

Do not take more than directed. See overdose warning

Drink a full glass of water with each dose

Adults and children 12 years and older

- Take 1 or 2 tablets every 4 hours or 3 tablets every 6 hours not to exceed 12 tablets in 24 hours unless directed by a doctor.

Children under 12 years

- Do not use unless directed by a doctor

Stop Use and ask a doctor if

- An allergic reaction occurs. Seek medical help right away
- You experience any of the following signs of stomach bleeding, feel faint, vomit blood, have bloody stools, have stomach pain that does not get better
- Ringing in the ears or loss of hearing occurs, pain gets worse or lasts more than 10 days, fever gets worse or lasts more than 3 days.
- New symptoms occur,
- Redness or swelling is present
- These could be signs of a serious condition

If pregnant or breast-feeding

Ask a health professional before use. It is especially important not to use aspirin at 20 weeks or later in pregnancy unless definitely directed to do so by a doctor because it may cause problems in the unborn child or complications during delivery.

Other Information

- Store at 25ºC (77ºF)
- Excursions permitted between 15ºC-30ºC (59ºF-86ºF)
- See end flap for expiration date and lot number
- Use by expiration date on package
- Tamper Evident: Do not use if packet is open or torn
- Read and Keep carton for complete warnings and information

Inactive Ingredients

Corn Starch, Hyperomelose, Polyethylene glycol, propylene glycol

Keep out of reach of children

In case of overdose, get medical help or contact a poison control center right away.

Questions or Comments?

Call 1-888-900-2920

Distributed By:

ProStat First Aid

La Verne, CA. USA

1-888-900-2920

*This product is not manufactured or distributed by the Bayer Healthcare LLC. owner of the registered trademark Bayer®

Made in the USA